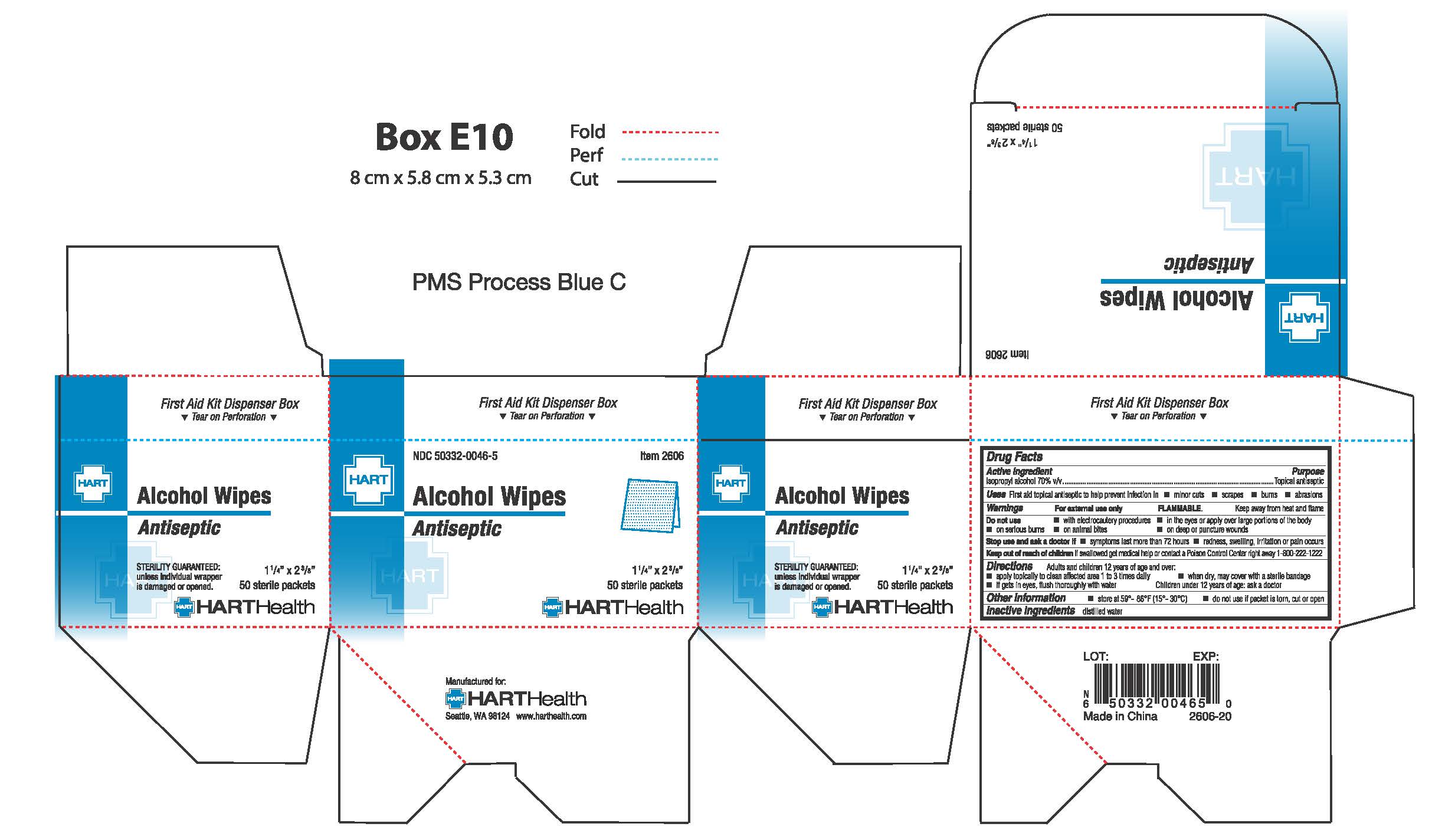 DRUG LABEL: Alcohol
NDC: 50332-0046 | Form: SWAB
Manufacturer: HART Health
Category: otc | Type: HUMAN OTC DRUG LABEL
Date: 20260112

ACTIVE INGREDIENTS: ISOPROPYL ALCOHOL .70 g/1 g
INACTIVE INGREDIENTS: WATER

ALCOHOL WIPES

Active Ingredient

Isopropyl Alcohol 70% v/v

Purpose

Topical Antiseptic

Uses

First aid topical antiseptic to help prevent infection in:

- minor cuts
- scrapes
- burns
- abrasions

Warnings

For external use only

FLAMMABLE keep away from heat and flame

Do not use

- with electrocautery procedures
- in the eyes or apply over large portions of the body
- on serious burns
- on animal bites
- on deep or puncture wounds

Stop use and ask a doctor if

- symptoms last more than 72 hours
- redness, swelling, irritation or pain occurs

Keep out of reach of children

If swallowed get medical help or contact Poison Control Center right away 1-800-222-1222

Directions

Adults and children 12 years of age and over

- apply topically to clean affected area 1 to 3 times daily
- when dry, may be covered with a sterile bandage
- if gets in eyes, flush thoroughly with water

Children under 12 years of age

- ask a doctor

Inactive Ingredient

Water